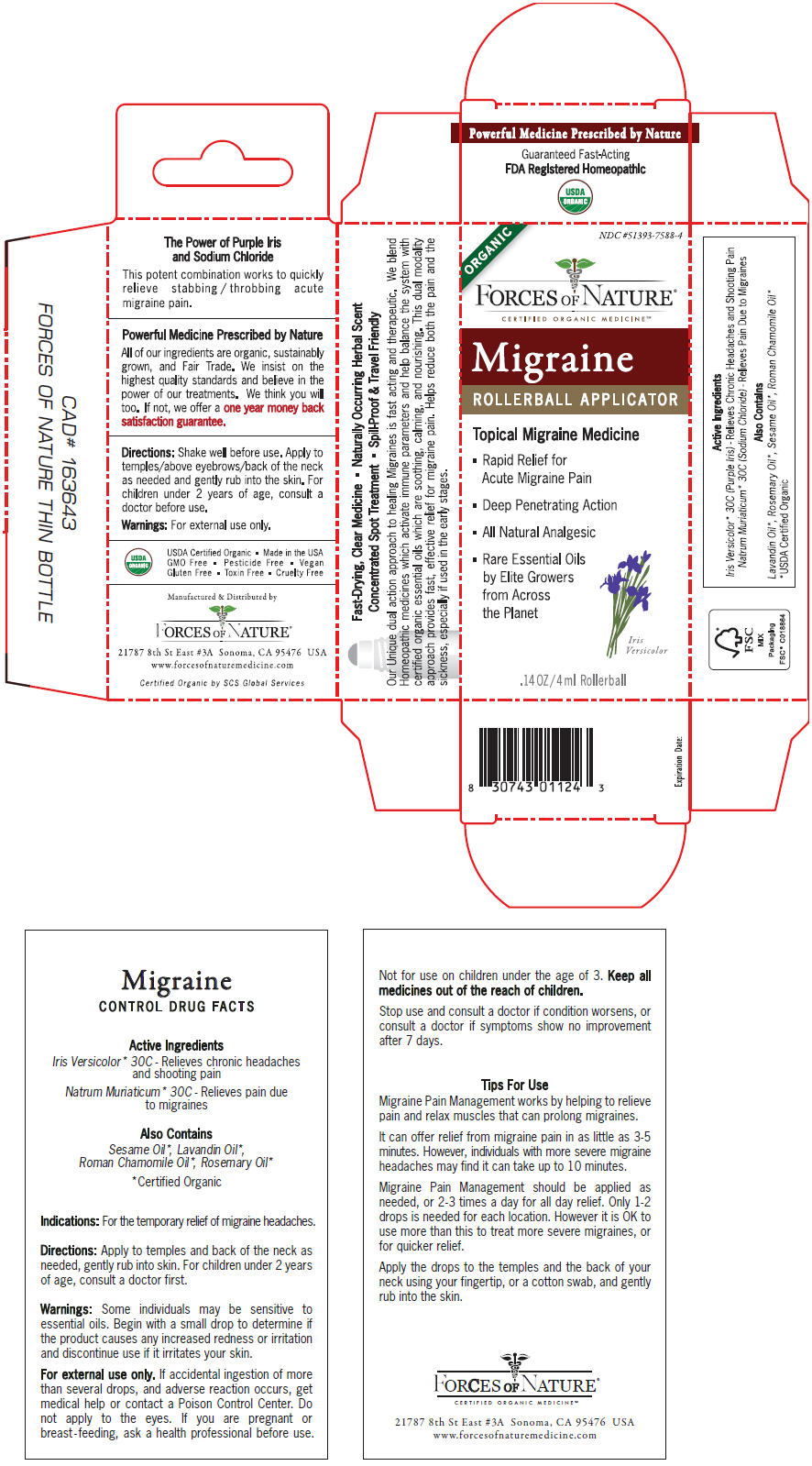 DRUG LABEL: Migraine 
NDC: 51393-7588 | Form: SOLUTION/ DROPS
Manufacturer: Forces of Nature
Category: homeopathic | Type: HUMAN OTC DRUG LABEL
Date: 20200427

ACTIVE INGREDIENTS: Iris Versicolor Root 30 [hp_X]/100 mL; Sodium Chloride 30 [hp_C]/100 mL
INACTIVE INGREDIENTS: Chamaemelum Nobile Flower Oil; Lavandin Oil; Rosemary Oil; Sesame Oil

Migraine
Pain Management

CONTROL DRUG FACTS

Active Ingredients

PURPOSE

Iris Versicolor [Certified Organic] 30C - Relieves chronic headaches and shooting pain

Natrum Muriaticum 30C - Relieves pain due to migraines

Also Contains

Sesame Oil, Lavandin Oil, Roman Chamomile Oil, Rosemary Oil

Indications

For the temporary relief of migraine headaches.

Directions

Apply to temples and back of the neck as needed, gently rub into skin. For children under 2 years of age, consult a doctor first.

Warnings

Some individuals may be sensitive to essential oils. Begin with a small drop to determine if the product causes any increased redness or irritation and discontinue use if it irritates your skin.

For external use only. If accidental ingestion of more than several drops, and adverse reaction occurs, get medical help or contact a Poison Control Center. Do not apply to the eyes. If you are pregnant or breast - feeding, ask a health professional before use. Not for use on children under the age of 3.

KEEP OUT OF REACH OF CHILDREN

Keep all medicines out of the reach of children.

Stop use and consult a doctor if condition worsens, or consult a doctor if symptoms show no improvement after 7 days.

Manufactured & Distributed by
FORCES OF NATURE®
21787 8th St East #3A Sonoma, CA 95476 USA

PRINCIPAL DISPLAY PANEL - 4 ml Bottle Carton

ORGANIC

NDC #51393-7588-4

FORCES OF NATURE®
CERTIFIED ORGANIC MEDICINESM

Migraine
ROLLERBALL APPLICATOR

Topical Migraine Medicine

- Rapid Relief for
  Acute Migraine Pain
- Deep Penetrating Action
- All Natural Analgesic
- Rare Essential Oils
  by Elite Growers
  from Across
  the Planet

Iris
Versicolor

.14 OZ/4 ml Rollerball